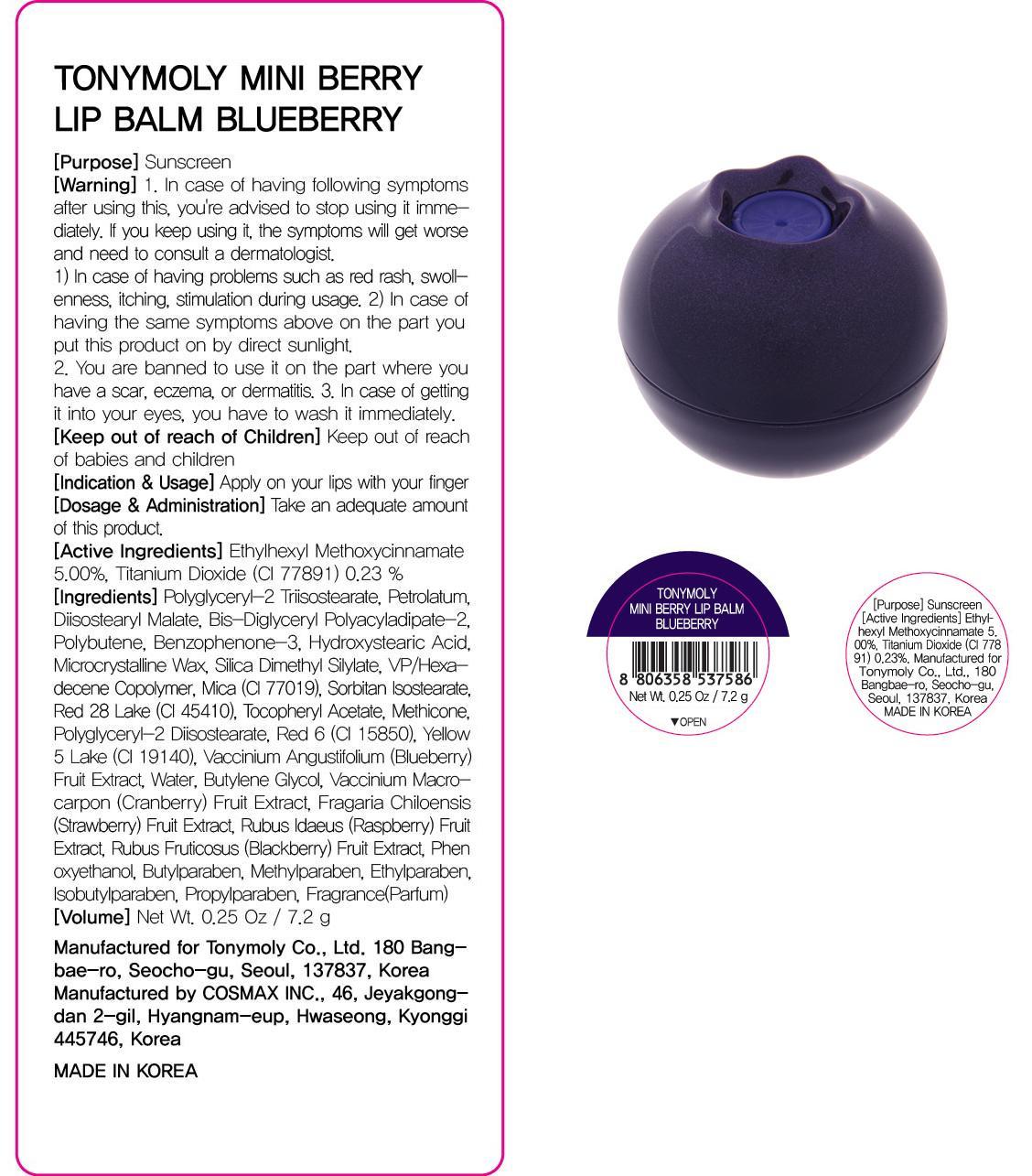 DRUG LABEL: MINI BERRY LIP BALM BLUEBERRY
NDC: 59078-038 | Form: CREAM
Manufacturer: TONYMOLY CO., LTD.
Category: otc | Type: HUMAN OTC DRUG LABEL
Date: 20150304

ACTIVE INGREDIENTS: OCTINOXATE 0.36 g/7.2 g; Titanium Dioxide 0.01 g/7.2 g
INACTIVE INGREDIENTS: Petrolatum; Diisostearyl Malate

ACTIVE INGREDIENT

Active ingredients: Ethylhexyl Methoxycinnamate 5.00%, Titanium Dioxide 0.23%

INACTIVE INGREDIENT

Inactive ingredients: Polyglyceryl-2 Triisostearate, Petrolatum, Diisostearyl Malate, Bis-Diglyceryl Polyacyladipate-2, Polybutene, Benzophenone-3, Hydroxystearic Acid, Microcrystalline Wax, Silica Dimethyl Silylate, VP/Hexadecene Copolymer, Mica (CI 77019), Sorbitan Isostearate, Red 28 Lake (CI 45410), Fragrance(Parfum), Butylparaben, Tocopheryl Acetate, Methicone, Polyglyceryl-2 Diisostearate, Red 6 (CI 15850), Yellow 5 Lake (CI 19140), Vaccinium Angustifolium (Blueberry) Fruit Extract, Water, Butylene Glycol, Vaccinium Macrocarpon (Cranberry) Fruit Extract, Fragaria Chiloensis (Strawberry) Fruit Extract, Rubus Idaeus (Raspberry) Fruit Extract, Rubus Fruticosus (Blackberry) Fruit Extract, Phenoxyethanol, Methylparaben, Ethylparaben, Isobutylparaben, Propylparaben

PURPOSE

PURPOSE: Sunscreen

WARNINGS

Warnings: 1. In case of having following symptoms after using this, you're advised to stop using it immediately. If you keep using it, the symptoms will get worse and need to consult a dermatologist. 1) In case of having problems such as red rash, swollenness, itching, stimulation during usage. 2) In case of having the same symptoms above on the part you put this product on by direct sunlight. 2. You are banned to use it on the part where you have a scar, eczema, or dermatitis. 3. In case of getting it into your eyes, you have to wash it immediately.

Keep out of reach of children: Keep out of reach of babies and children

INDICATIONS & USAGE

INDICATIONS AND USAGE: Apply on lip with fingers

DOSAGE & ADMINISTRATION

DOSAGE AND ADMINISTRATION: Take an adequate amount of this product.

PACKAGE LABEL.PRINCIPAL DISPLAY PANEL

Image of carton